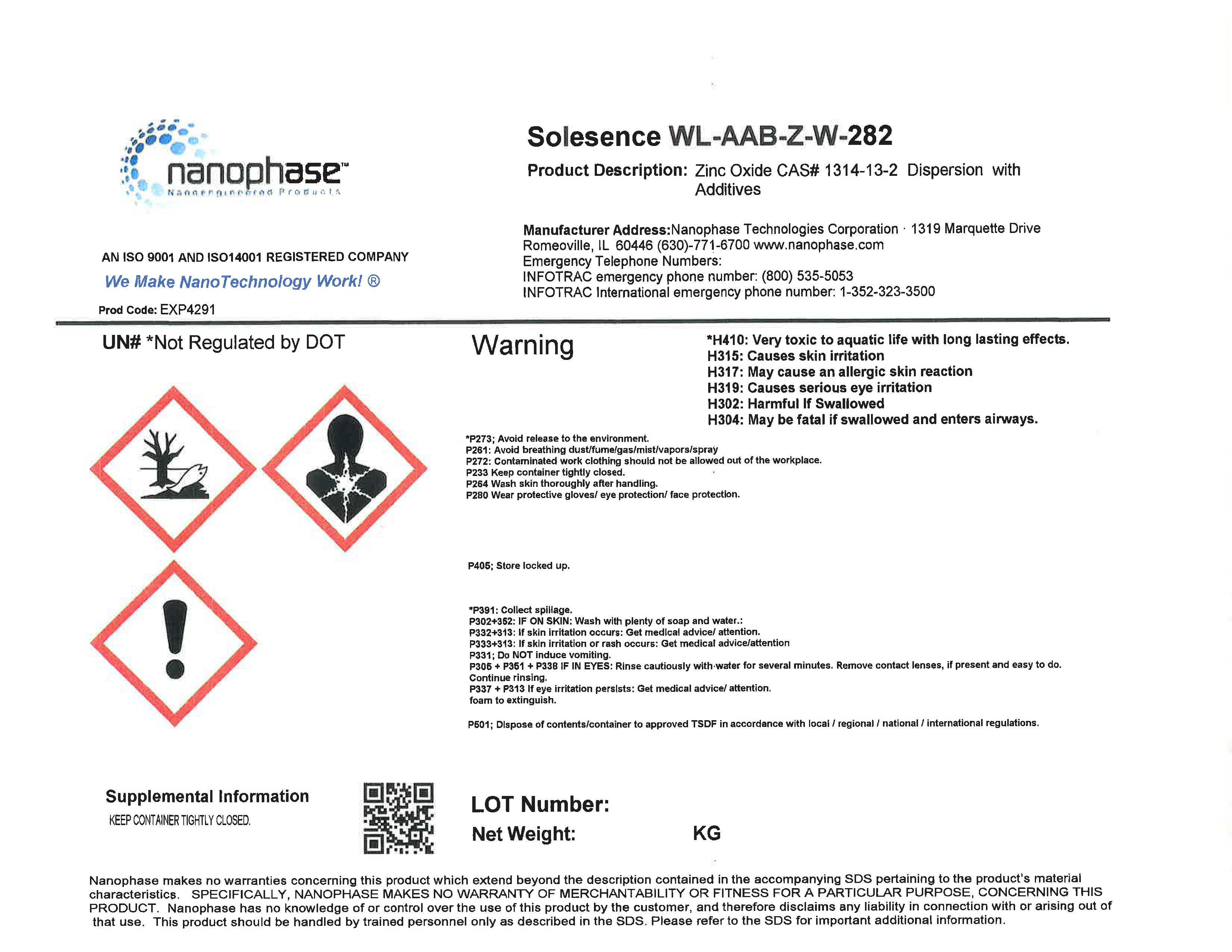 DRUG LABEL: WL-AAB-Z-W-330
NDC: 63931-4291 | Form: LOTION
Manufacturer: Nanophase Technologies Corporation
Category: otc | Type: HUMAN OTC DRUG LABEL
Date: 20190722

ACTIVE INGREDIENTS: ZINC OXIDE 132 mg/1 mL
INACTIVE INGREDIENTS: PALMITOYL TETRAPEPTIDE-7; TRILAURETH-4 PHOSPHATE; BUTYLOCTYL SALICYLATE; OCTYLDODECYL NEOPENTANOATE; ISODODECANE; .ALPHA.-BISABOLOL, (+)-; BUTYLENE GLYCOL; POLYSORBATE 20; SODIUM HYDROXIDE; WATER; NIACINAMIDE; ETHYLHEXYLGLYCERIN; HEXYLENE GLYCOL; GLYCERIN; DIMETHICONOL/PROPYLSILSESQUIOXANE/SILICATE CROSSPOLYMER (450000000 MW); PROPANEDIOL; TETRASODIUM GLUTAMATE DIACETATE; CARRAGEENAN; SODIUM CHLORIDE; PHENOXYETHANOL; PALMITOYL TRIPEPTIDE-1; .BETA.-TOCOPHEROL; POLYMETHYLSILSESQUIOXANE (4.5 MICRONS)

WL-AAB-Z-W-282